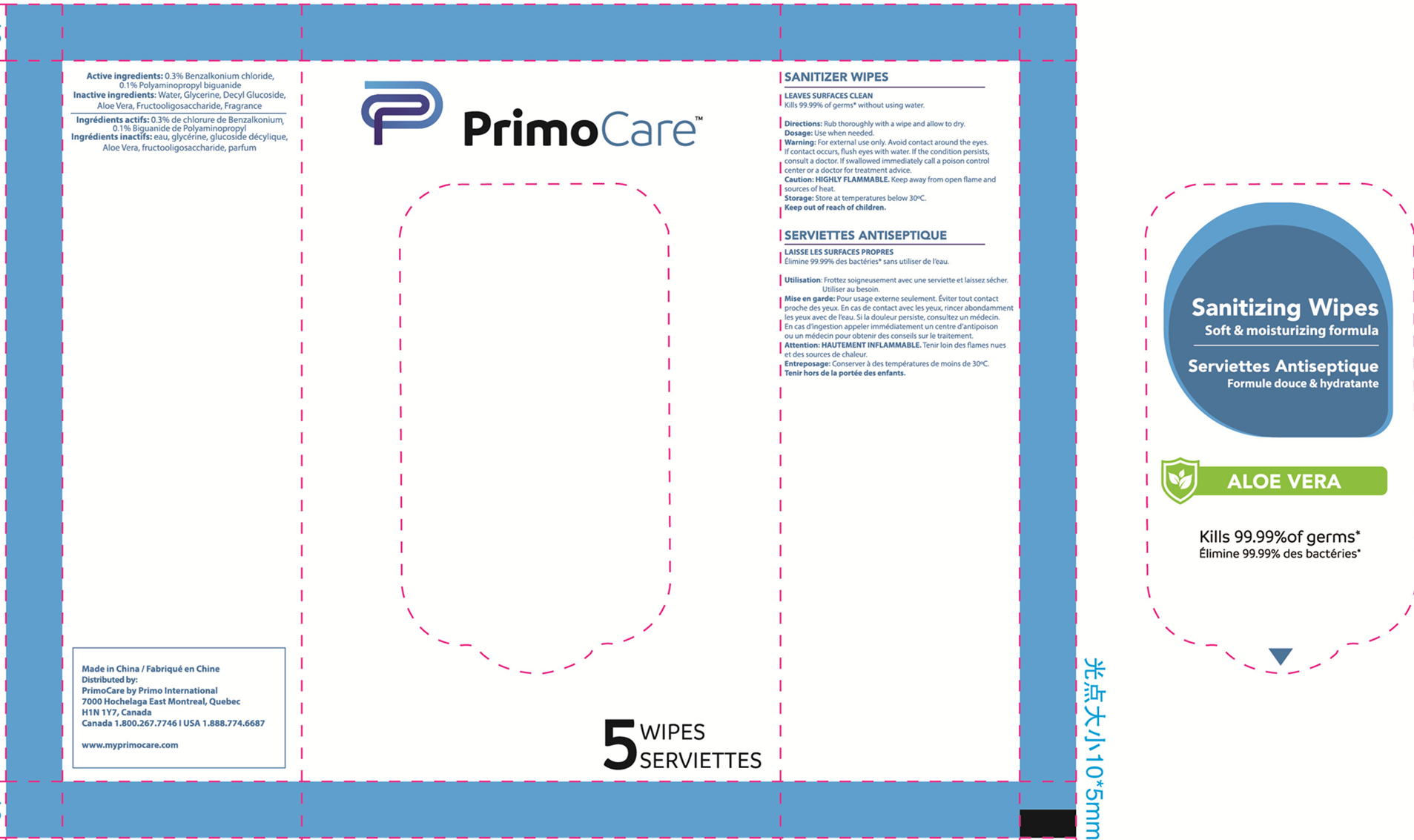 DRUG LABEL: Sanitizing wipes
NDC: 79795-004 | Form: CLOTH
Manufacturer: NanTong Guarder Medical Technology Co.,Ltd.
Category: otc | Type: HUMAN OTC DRUG LABEL
Date: 20201109

ACTIVE INGREDIENTS: POLYAMINOPROPYL BIGUANIDE 0.1 g/100 1; BENZALKONIUM CHLORIDE 0.3 g/100 1
INACTIVE INGREDIENTS: DECYL GLUCOSIDE; ALOE VERA LEAF; GLYCERIN; WATER

Sanitizing wipes

Active Ingredient(s)

Benzalkonium chloride 0.3% w/v

Polyaminopropyl biguanide 0.1% w/v.

Purpose: Antiseptic

Purpose

Antiseptic

Use

- For hand and skin cleaning
- Recommended for repeated use
- For use when soap and water are not available

Warnings

For external use only. Avoid contact around the eyes. If contact occurs, flush eyes with water. If the condition persists, consult a doctor. If swallowed immediately call a poison control center or a doctor for treatment advice.

Do not use

- in children less than 2 months of age
- on open skin wounds

When using this product keep out of eyes, ears, and mouth. In case of contact with eyes, rinse eyes thoroughly with water.
Stop use and ask a doctor if irritation or rash occurs. These may be signs of a serious condition.
Keep out of reach of children. If swallowed, get medical help or contact a Poison Control Center right away.

Stop use and ask a doctor if irritation or rash occurs. These may be signs of a serious condition.

Keep out of reach of children. If swallowed, get medical help or contact a Poison Control Center right away.

Directions

Wet hands thoroughly with product and allow to dry.

Dicard wipes in trash receptacle after use. Do not flush.

Children under 6 years of age should be supervised when using this product.

Other information

- Store between 15-30C (59-86F)
- Avoid freezing and excessive heat above 40C (104F)

Inactive ingredients

Water, Glycerine, Decyl Glucoside, Aloe Vera, Fructooligosaccharide, Fragrance

Package Label - Principal Display Panel

5wipes in one box NDC:79795-004-02